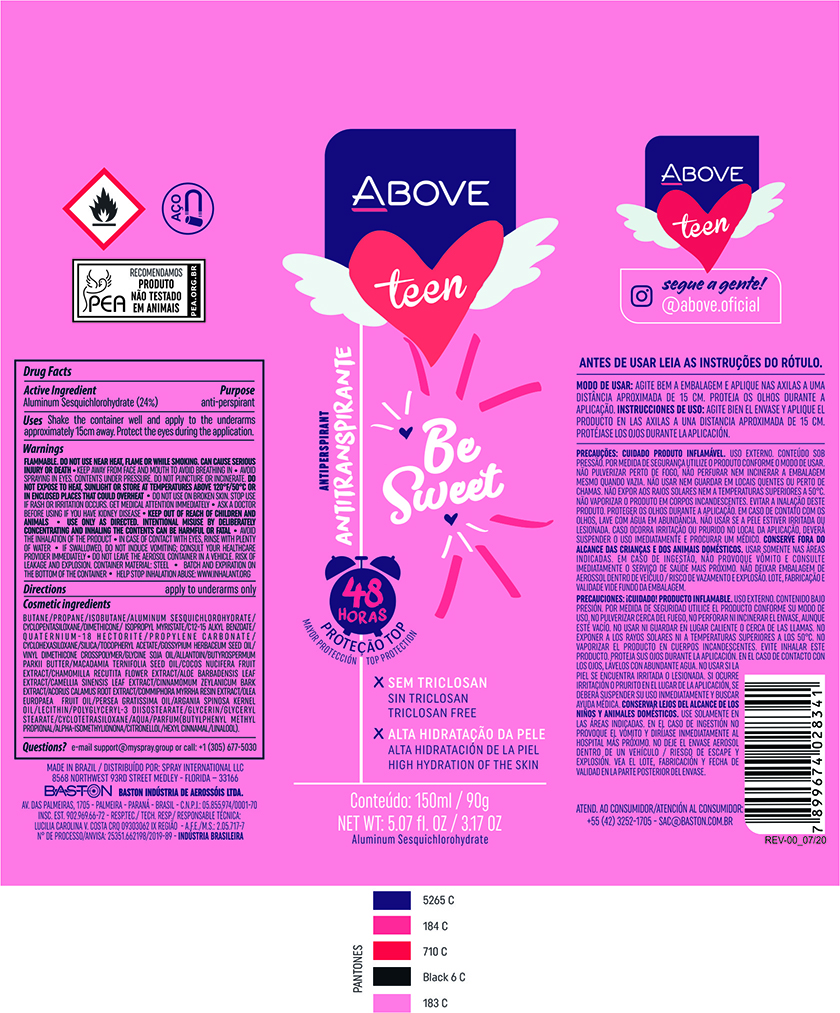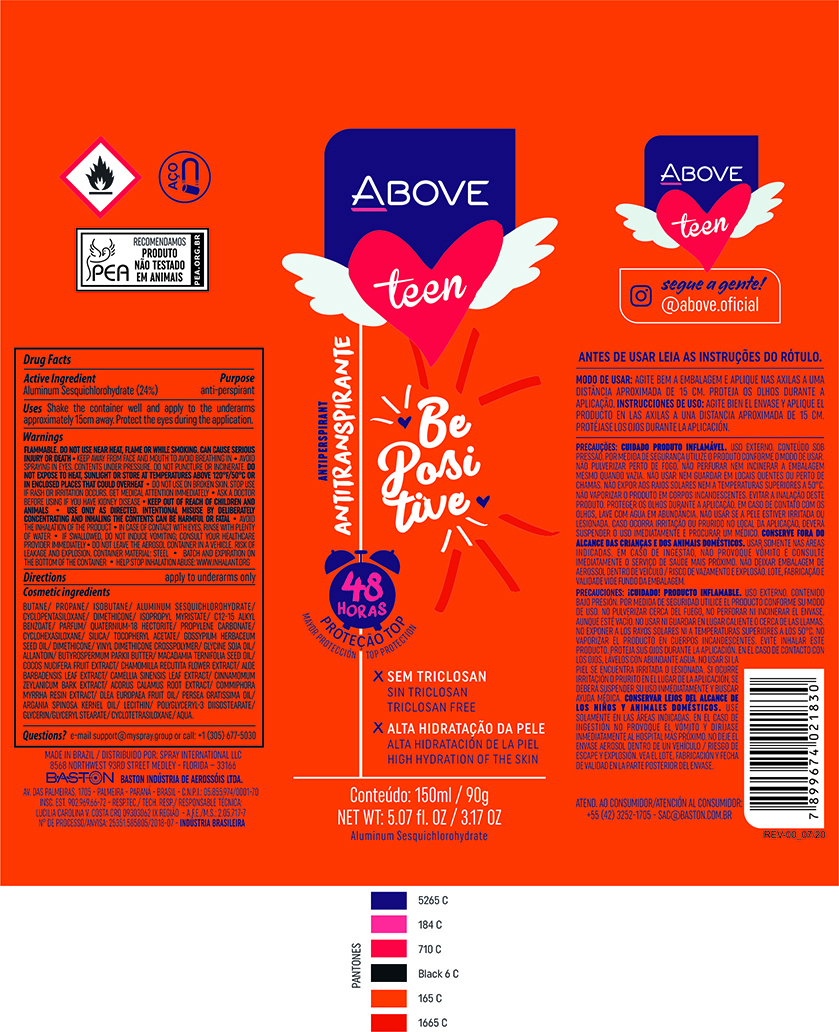 DRUG LABEL: Antiperspirant Above Teen Be Sweet
NDC: 73306-1126 | Form: AEROSOL, SPRAY
Manufacturer: Baston Industria de Aerossóis Ltda
Category: otc | Type: HUMAN OTC DRUG LABEL
Date: 20241226

ACTIVE INGREDIENTS: ALUMINUM SESQUICHLOROHYDRATE 24 g/100 g
INACTIVE INGREDIENTS: PROPYLENE CARBONATE; CHAMOMILE; AVOCADO OIL; LECITHIN, SOYBEAN; MYRRH OIL; ALOE VERA LEAF; DIMETHICONE; LEVANT COTTON SEED; SILICA DIMETHYL SILYLATE; BUTANE; ISOBUTANE; PROPANE; DISTEARDIMONIUM HECTORITE; CYCLOMETHICONE 5; ARGAN OIL; VINYL DIMETHICONE/METHICONE SILSESQUIOXANE CROSSPOLYMER; .ALPHA.-TOCOPHEROL ACETATE; COCONUT; GLYCERYL MONOSTEARATE; MACADAMIA OIL; ISOPROPYL MYRISTATE; GREEN TEA LEAF; CINNAMON BARK OIL; SHEA BUTTER; WATER; POLYGLYCERYL-3 DIISOSTEARATE

Antiperspirant Above Teen Be Sweet

Aluminum sesquichlorohydrate 24%

INACTIVE INGREDIENT

BUTANE/PROPANE/ISOBUTANE/ALUMINUM SESQUICHLOROHYDRATE/CYCLOPENTASILOXANE/DIMETHICONE/
ISOPROPYL MYRISTATE/C12-15 ALKYL BENZOATE/QUATERNIUM-18 HECTORITE/PROPYLENE CARBONATE/CYCLOHEXASILOXANE/SILICA/TOCOPHERYL ACETATE/GOSSYPIUM HERBACEUM SEED OIL/VINYL DIMETHICONE CROSSPOLYMER/GLYCINE SOJA OIL/ALLANTOIN/BUTYROSPERMUM PARKII BUTTER/
MACADAMIA TERNIFOLIA SEED OIL/COCOS NUCIFERA FRUIT EXTRACT/CHAMOMILLA RECUTITA FLOWER EXTRACT/ALOE BARBADENSIS LEAF EXTRACT/CAMELLIA SINENSIS LEAF EXTRACT/CINNAMOMUM ZEYLANICUM BARK EXTRACT/ACORUS CALAMUS ROOT EXTRACT/COMMIPHORA MYRRHA RESIN EXTRACT/OLEA EUROPAEA FRUIT OIL/PERSEA GRATISSIMA OIL/ARGANIA SPINOSA KERNEL OIL/LECITHIN/POLYGLYCERYL-3 DIISOSTEARATE/GLYCERIN/GLYCERYL STEARATE/
CYCLOTETRASILOXANE/AQUA/PARFUM(BUTYLPHENYL METHYL PROPIONAL/ALPHA-ISOMETHYLIONONA/CITRONELLOL/HEXYL CINNAMAL/LINALOOL).

INDICATIONS AND USAGE

Uses - reduces underarm wetness

DOSAGE AND ADMINISTRATION

apply to underarms only

QUESTIONS

e-mail: support@myspray.group or call:+1(305)677-5030

Keep Out Of Reach Of Children

WARNINGS AND PRECAUTIONS

Flammable until fully dry. Do not use near heat, Flame or while smoking. Can cause serious injury or deat•Keep away from face and mouth to avoid breathing in•Avoid spraying in eyes•Contents under pressure•Do not puncture or incinerate•Do not expose to heat or store at temperatures above 120 ºF/50 ºC or in enclosed places that could overheat•Do not use on broken skin•Stop use if rash or irritation occurs•Ask a doctor before using if you have kidney disease•USE ONLY AS DIRECTED•INTENTIONAL MISUSE BY DELIBERATELY CONCENTRATING AND INHALING THE CONTENTS CAN BE HARMFUL OR FATAL•Avoid de inhalation of the product.

PURPOSE

Antiperspirant